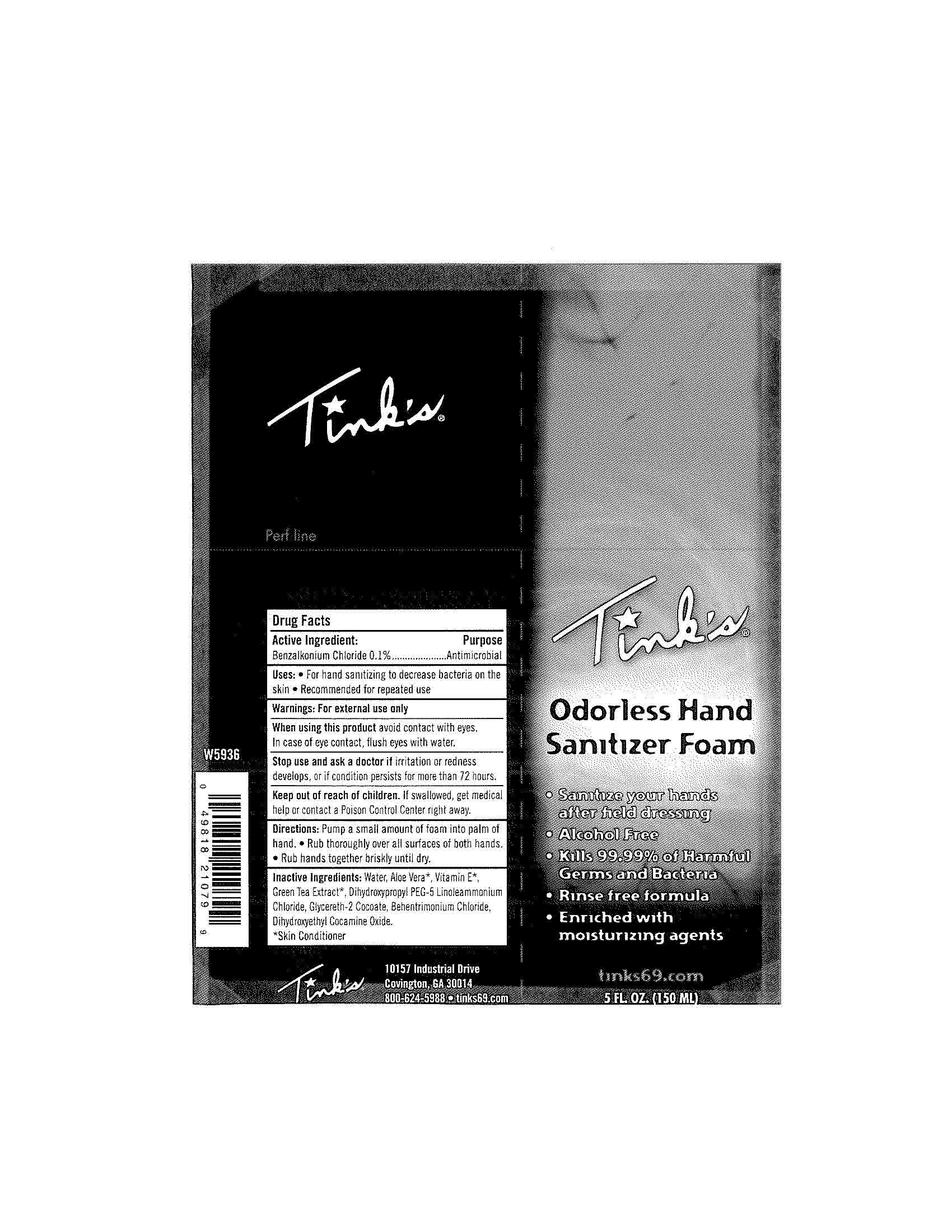 DRUG LABEL: Odorless Hand Sanitizer Foam
NDC: 52473-010 | Form: LIQUID
Manufacturer: Tinks
Category: otc | Type: HUMAN OTC DRUG LABEL
Date: 20100823

ACTIVE INGREDIENTS: Benzalkonium Chloride 0.1 mL/100 mL
INACTIVE INGREDIENTS: Water; Aloe Vera Leaf; DIHYDROXYPROPYL PEG-5 LINOLEAMMONIUM CHLORIDE; Glycereth-2 Cocoate; Behentrimonium Chloride; Dihydroxyethyl Cocamine Oxide

Drug Facts

Active Ingredient

Benzalkonium Chloride 0.1%

Purpose

Antimicrobial

Uses

For Hand sanitizing to decrease bacteria on the skin

Recommended for repeated uses

Warnings

For external use only

When using this product avoid contact with eyes. In case of eye contact,flush eyes with water.

Stop use and ask a doctor if irritation or redness develops, or if condition persists for more than 72 hours.

KEEP OUT OF REACH OF CHILDREN

If swallowed, get medical help or contact a Poison Control Center right away.

Directions

Pump a small amount of foam into palm of hand. Rub thoroughly over all surfaces of both hands. Rub hands together briskly until dry.

Inactive Ingredients

Water, Aloe Vera*, Vitamin E*, Green Tea Extract*, Dihydroxypropyl PEG-5 Linoleamonium Chloride, Glycereth-2 Cocoate, Behentrimonium Chloride, Dihydroxyethyl Cocamine Oxide.

*Skin Conditioner

PACKAGE LABEL

Tink's

Odorless Hand

Sanitizer Foam

Sanitize your hands after field dressing

Alcohol Free

Kills 99.99% of Harmful Germs and Bacteria

Rinse free formula

Enriched with moisturizing agents

tinks69.com

5 FL. OZ. (150 ML)